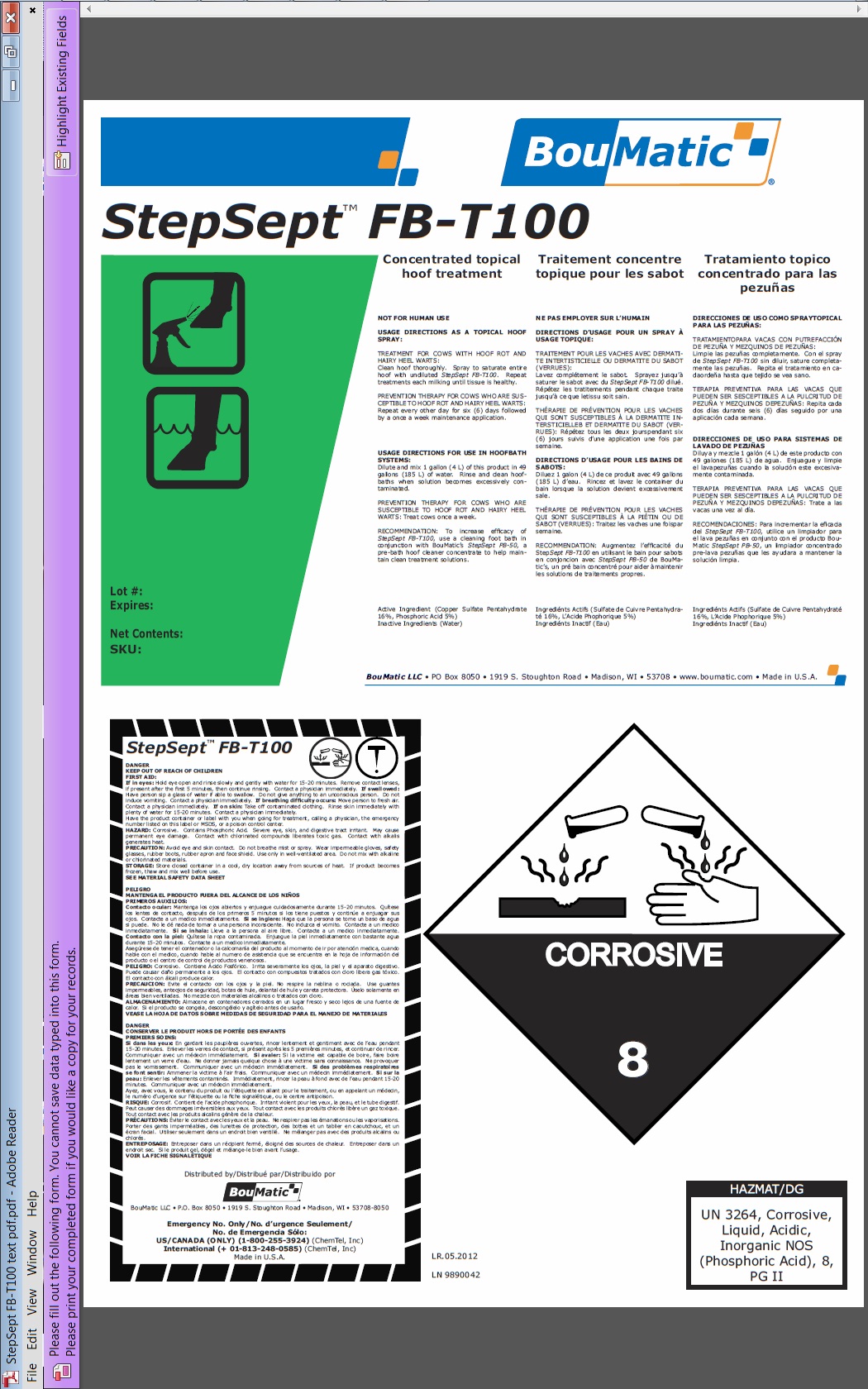 DRUG LABEL: StepSept FB-T100
NDC: 48106-1149 | Form: LIQUID
Manufacturer: BouMatic, LLC
Category: animal | Type: OTC ANIMAL DRUG LABEL
Date: 20120101

ACTIVE INGREDIENTS: CUPRIC SULFATE 1600 mL/10 L; PHOSPHORIC ACID 375 mL/10 L

StepSept FB-T100

INDICATIONS AND USAGE

Concentrated topical hoof treatment
NOT FOR HUMAN USE
USAGE DIRECTIONS AS A TOPICAL HOOF SPRAY:
TREATMENT FOR COWS WITH HOOF ROT AND HAIRY HEEL WARTS:
Clean hoof thoroughly. Spray to saturate entire hoof with undiluted StepSept FB-T100. Repeat treatments each milking until tissue is healthy.
PREVENTION THERAPY FOR COWS WHO ARE SUSCEPTIBLE TO HOOF ROT AND HAIRY HEEL WARTS: Repeat every other day for six (6) days followed by a once a week maintenance application.
USAGE DIRECTIONS FOR USE IN HOOFBATH SYSTEMS:
Dilute and mix 1 gallon (4 L) of this product in 49 gallons (185 L) of water. Rinse and clean hoofbaths when solution becomes excessively contaminated.
PREVENTION THERAPY FOR COWS WHO ARE SUSCEPTIBLE TO HOOF ROT AND HAIRY HEEL WARTS: Treat cows once a week.
RECOMMENDATION: To increase efficacy of StepSept FB-T100, use a cleaning foot bath in conjunction with BouMatic’s StepSept PB-50, a pre-bath hoof cleaner concentrate to help maintain clean treatment solutions.
Active Ingredient (Copper Sulfate Pentahydrate 16%, Phosphoric Acid 5%)
Inactive Ingredients (Ethanol, Water)

PRECAUTIONS

DANGER
KEEP OUT OF REACH OF CHILDREN
FIRST AID:
If in eyes: Hold eye open and rinse slowly and gently with water for 15-20 minutes. Remove contact lenses, if present after the first 5 minutes, then continue rinsing. Contact a physician immediately. If swallowed: Have person sip a glass of water if able to swallow. Do not give anything to an unconscious person. Do not induce vomiting. Contact a physician immediately. If breathing difficulty occurs: Move person to fresh air. Contact a physician immediately. If on skin: Take off contaminated clothing. Rinse skin immediately with plenty of water for 15-20 minutes. Contact a physician immediately.
Have the product container or label with you when going for treatment, calling a physician, the emergency number listed on this label or MSDS, or a poison control center.
HAZARD: Corrosive. Contains Phosphoric Acid. Severe eye, skin, and digestive tract irritant. May cause permanent eye damage. Contact with chlorinated compounds liberates toxic gas. Contact with alkalis generates heat.
PRECAUTION: Avoid eye and skin contact. Do not breathe mist or spray. Wear impermeable gloves, safety glasses, rubber boots, rubber apron and face shield. Use only in well-ventilated area. Do not mix with alkaline or chlorinated materials.
STORAGE: Store closed container in a cool, dry location away from sources of heat. If product becomes frozen, thaw and mix well before use.
SEE MATERIAL SAFETY DATA SHEET